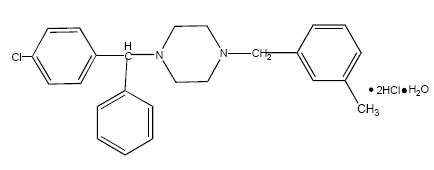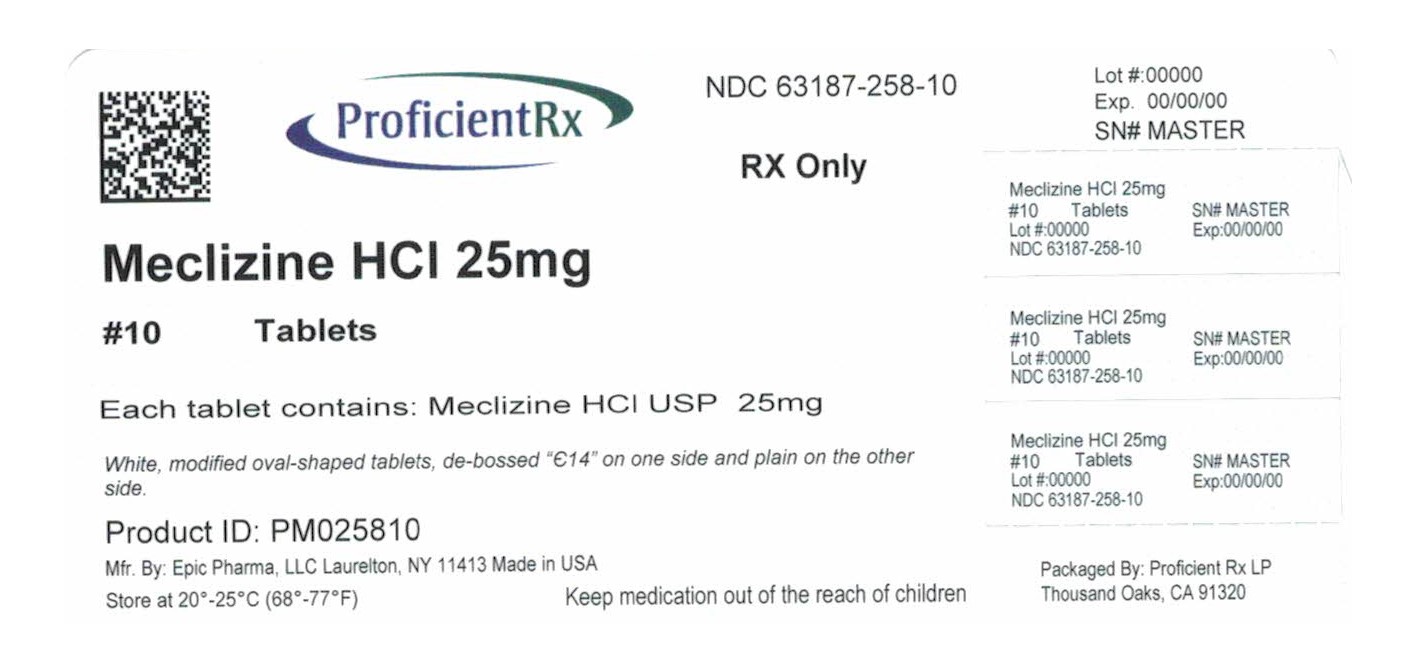 DRUG LABEL: Meclizine Hydrochloride
NDC: 63187-258 | Form: TABLET
Manufacturer: Proficient Rx LP
Category: prescription | Type: HUMAN PRESCRIPTION DRUG LABEL
Date: 20210101

ACTIVE INGREDIENTS: MECLIZINE HYDROCHLORIDE 25 mg/1 1
INACTIVE INGREDIENTS: MICROCRYSTALLINE CELLULOSE; LACTOSE MONOHYDRATE; CROSCARMELLOSE SODIUM; MAGNESIUM STEARATE

Meclizine Hydrochloride Tablets USP, 12.5 mg and 25 mg
Rx Only

DESCRIPTION

Chemically, meclizine hydrochloride is 1-(p-chloro-α-phenylbenzyl)-4-(m-methylbenzyl) piperazine dihydrochloride monohydrate.

C25H27CIN2·2HCl·H20 M.W. 481.89

Meclizine hydrochloride tablets, USP are available in two different strengths, 12.5 mg and 25 mg. Inactive ingredients: microcrystalline cellulose, lactose monohydrate, croscarmellose sodium and magnesium stearate. The 12.5 mg tablet also contains FD&C Blue #1 Aluminum Lake.

CLINICAL PHARMACOLOGY

Meclizine hydrochloride is an antihistamine that shows marked protective activity against nebulized histamine and lethal doses of intravenously injected histamine in guinea pigs. It has a marked effect in blocking the vasodepressor response to histamine, but only a slight blocking action against acetylcholine. Its activity is relatively weak in inhibiting the spasmogenic action of histamine on isolated guinea pig ileum.

Pharmacokinetics

The available pharmacokinetic information for meclizine following oral administration has been summarized from published literature.

Absorption

Meclizine is absorbed after oral administration with maximum plasma concentrations reaching at a median Tmax value of 3 hours post-dose (range: 1.5 to 6 hours) for the tablet dosage form.

Distribution

Drug distribution characteristics for meclizine in humans are unknown.

Metabolism

The metabolic fate of meclizine in humans is unknown. In an in vitro metabolic study using human hepatic microsome and recombinant CYP enzyme, CYP 2D6 was found to be the dominant enzyme for metabolism of meclizine.

The genetic polymorphism of CYP2D6 that results in extensive-, poor-, intermediate- and ultrarapid metabolizer phenotypes could contribute to large inter-individual variability in meclizine exposure.

Elimination

Meclizine has a plasma elimination half-life of about 5-6 hours in humans.

INDICATIONS

BOXED WARNING

Based on a review of this drug by the National Academy of Sciences - National Research Council and/or other information, FDA has classified the indications as follows:

Effective: Management of nausea and vomiting, and dizziness associated with motion sickness.

Final classification of the less than effective indications requires further investigation.

CONTRAINDICATIONS

Meclizine hydrochloride is contraindicated in individuals who have shown a previous hypersensitivity to it.

WARNINGS

Since drowsiness may, on occasion, occur with use of this drug, patients should be warned of this possibility and cautioned against driving a car or operating dangerous machinery.

Patients should avoid alcoholic beverages while taking this drug.

Due to its potential anticholinergic action, this drug should be used with caution in patients with asthma, glaucoma, or enlargement of the prostate gland.

Usage in Children

Clinical studies establishing safety and effectiveness in children have not been done; therefore, usage is not recommended in children under 12 years of age.

Usage in Pregnancy

Pregnancy Category B

Reproduction studies in rats have shown cleft palates at 25-50 times the human dose. Epidemiological studies in pregnant women, however, do not indicate that meclizine increases the risk of abnormalities when administered during pregnancy. Despite the animal findings, it would appear that the possibility of fetal harm is remote. Nevertheless, meclizine, or any other medication, should be used during pregnancy only if clearly necessary.

PRECAUTIONS

Nursing Mothers

It is not known whether this drug is excreted in human milk. Because many drugs are excreted in human milk, caution should be exercised when meclizine is administered to a nursing woman.

Hepatic Impairment

The effect of hepatic impairment on the pharmacokinetics of meclizine has not been evaluated. As meclizine undergoes metabolism, hepatic impairment may result in increased systemic exposure of the drug. Treatment with meclizine should be administered with caution in patients with hepatic impairment.

Renal Impairment

The effect of renal impairment on the pharmacokinetics of meclizine has not been evaluated. Due to a potential drug/metabolite accumulation, meclizine should be administered with caution in patients with renal impairment and in the elderly as renal function generally declines with age.

Drug Interactons

There may be increased CNS depression when meclizine is administered concurrently with other CNS depressants, including alcohol, tranquilizers, and sedatives. (see WARNINGS)

Based on in-vitro evaluation, meclizine is metabolized by CYP2D6. Therefore there is a possibility for a drug interaction between meclizine and CYP2D6 inhibitors.

ADVERSE REACTIONS

Anaphylactoid reaction, drowsiness, dry mouth, headache, fatigue, vomiting and, on rare occasions, blurred vision have been reported.

DOSAGE AND ADMINISTRATION

Motion Sickness

The initial dose of 25 to 50 mg of meclizine hydrochloride should be taken one hour prior to embarkation for protection against motion sickness. Thereafter, the dose may be repeated every 24 hours for the duration of the journey.

HOW SUPPLIED

Meclizine Hydrochloride Tablets USP are available as:

25 mg, white, modified oval-shaped tablets, de-bossed “Є14” on one side and plain on the other side. They are supplied as follows:

NDC 63187-258-10 in bottles of 10

NDC 63187-258-20 in bottles of 20

NDC 63187-258-30 in bottles of 30

NDC 63187-258-60 in bottles of 60

NDC 63187-258-90 in bottles of 90

Store at 20º to 25ºC (68 to 77ºF) [See USP Controlled Room Temperature]. Dispense contents in a tight, light-resistant container as defined in the USP, with a child-resistant closure, as required.

Manufactured by:

Epic Pharma, LLC

Laurelton, NY 11413

Made in USA

Revised April 2014

MF012REV04/14

OE1035

Repackaged by:
Proficient Rx LP
Thousand Oaks, CA 91320